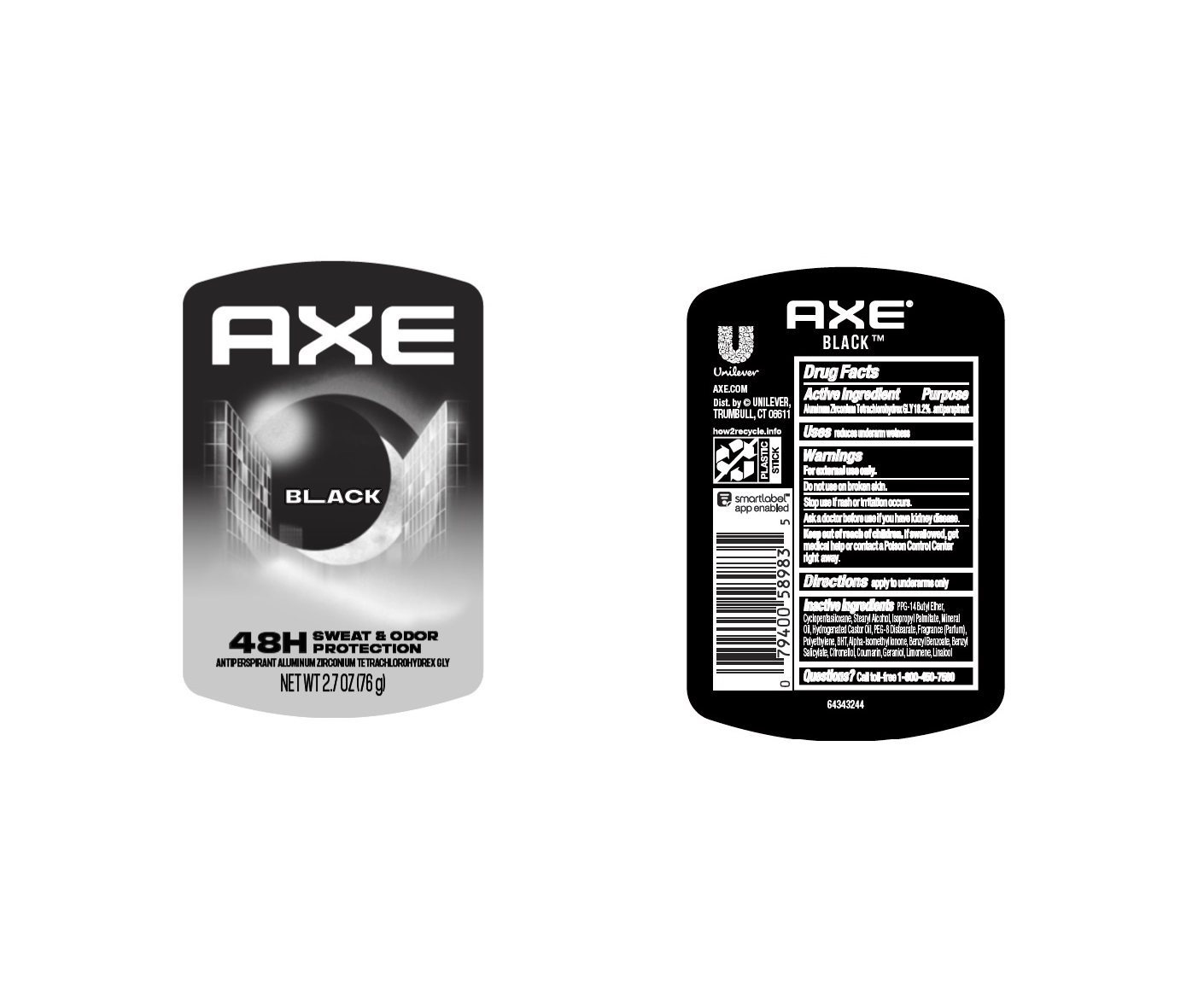 DRUG LABEL: Axe
NDC: 64942-2351 | Form: STICK
Manufacturer: Conopco Inc. d/b/a/ Unilever
Category: otc | Type: HUMAN OTC DRUG LABEL
Date: 20240926

ACTIVE INGREDIENTS: ALUMINUM ZIRCONIUM TETRACHLOROHYDREX GLY 18.2 g/100 g
INACTIVE INGREDIENTS: LIMONENE, (+)-; GERANIOL; CYCLOMETHICONE 5; HYDROGENATED CASTOR OIL; BUTYLATED HYDROXYTOLUENE; STEARYL ALCOHOL; PPG-14 BUTYL ETHER; MINERAL OIL; PEG-8 DISTEARATE; ISOPROPYL PALMITATE; HIGH DENSITY POLYETHYLENE; LINALOOL, (+/-)-; COUMARIN; ISOMETHYL-.ALPHA.-IONONE; BENZYL BENZOATE; BENZYL SALICYLATE; .BETA.-CITRONELLOL, (R)-

Axe Black 48H Sweat & Odor Protection Antiperspirant

AXE BLACK 48H SWEAT & ODOR PROTECTION ANTIPERSPIRANT - aluminum zirconium tetrachlorohydrex gly stick

Axe Dark Temptation 48H Anti Sweat Antiperspirant

Drug Facts

Active ingredient

Aluminum Zirconium Tetrachlorohydrex GLY (18.2 %)

Purpose

antiperspirant

Uses

reduces underarm wetness

Warnings

For externaluse only

Do not use on broken skin

Stop use if rash or irritation occurs
Ask a doctor before use if you have kidney disease

Keep out of reach of children.

If swallowed, get medical help or contact a Poison Control Center right away.

Directions

apply to underarms only

Inactive ingredients

PPG-14 Butyl Ether, Cyclopentasiloxane, Stearyl Alcohol, Isopropyl Palmitate, Mineral Oil, Hydrogenated Castor Oil, PEG-8 Distearate, Fragrance (Parfum), Polyethylene, BHT, Alpha-Isomethyl Ionone, Benzyl Benzoate, Benzyl Salicylate, Citronellol, Coumarin, Geraniol, Limonene, Linalool

Questions?

Call toll-free 1-800-450-7580